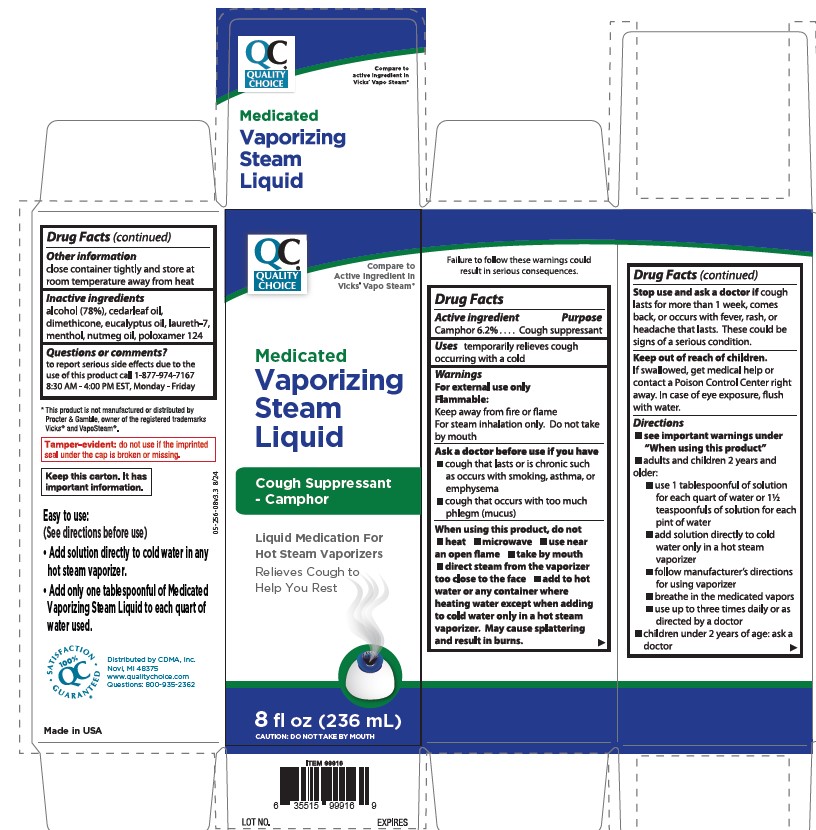 DRUG LABEL: Quality Choice Vapor Steam
NDC: 83324-266 | Form: LIQUID
Manufacturer: Chain Drug Marketing Association, Inc.
Category: otc | Type: HUMAN OTC DRUG LABEL
Date: 20251112

ACTIVE INGREDIENTS: CAMPHOR (SYNTHETIC) 0.623 g/10 mL
INACTIVE INGREDIENTS: ALCOHOL; CEDAR LEAF OIL; EUCALYPTUS OIL; LAURETH-7; MENTHOL; NUTMEG OIL; POLOXAMER 124; DIMETHICONE

Quality Choice Medicated Vaporizing Steam Liquid

ACTIVE INGREDIENT

Camphor 6.2%

PURPOSE

Cough suppressant

Use

temporarily relieves cough ocurring with a cold

WARNINGS

For external use only

Flammable: Keep away from fire or flame

For steam inhalation only. Do not take by mouth

For external use only.

Flammable. Keep away from fire or flame.

For steam inhalation only.

ASK DOCTOR

• a cough that lasts or is chronic such as occurs with smoking, asthma, or emphysema

• cough that ocurs with too much phlegm (mucus)

Do not use

- heat
- microwave
- use near an open flame
- take by mouth
- direct steam from the vaporizer too close to the face
- add to hot water or any container where heating water except when adding to cold water only in a hot steam vaporizer. May cause splattering and result in burns.

Stop use and ask a doctor if cough lasts more than 7 days, comes back, or occurs with fever, rash, or headache that lasts. These could be signs of a serious condition.

KEEP OUT OF REACH OF CHILDREN

If swallowed, get medical help or contact a Poison Control Center right away. In case of eye exposure, flush with water.

DOSAGE AND ADMINISTRATION

- see important warnings under "When using this product"
- adults & children 2 years & over:
- use 1 tablespoon of solution for each quart of water or 1½ teaspoonful of solution for each pint of water
- add solution directly to cold water only in a hot steam vaporizer
- follow manufacturer's directions for using vaporizer
- breathe in the medicated vapors
- use up to three times daily or as directed by a doctor
- children under 2 years: ask a doctor

STORAGE AND HANDLING

- close container tightly and store at room temperature away from heat

INACTIVE INGREDIENT

alcohol (78%), cedarleaf oil, dimethicone, eucalyptus oil, laureth-7, menthol, nutmeg oil, poloxamer 124

RECENT MAJOR CHANGES

Boxed Warning
• Indications and Usage
• Dosage and Administration
• Contraindications
• Warnings and Precautions

Removed title section as it repeated section type

PACKAGE LABEL

Quality Choice

Compare to the active ingredient in Vicks ® VapoSteam ®*

MEDICATED VAPORIZING STEAM LIQUID

COUGH SUPPRESSANT CONTAINS CAMPHOR

Liquid Medication for Hot Steam Vaporizers

Relieves Cough to Help You Rest

CAUTION: NOT FOR INTERNAL USE